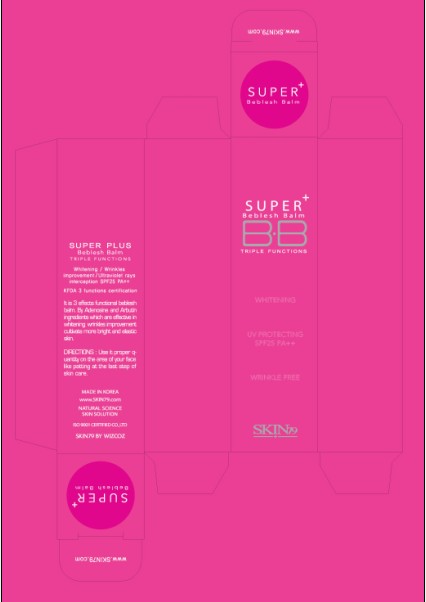 DRUG LABEL: SKIN79 Super Plus Beblesh Balm Triple Functions SPF25 PA (5g)
NDC: 49715-003 | Form: CREAM
Manufacturer: WIZCOZ CORPORATION LTD
Category: otc | Type: HUMAN OTC DRUG LABEL
Date: 20091109

ACTIVE INGREDIENTS: ZINC OXIDE 0.1 g/5 g; OCTISALATE 0.1 g/5 g; OCTINOXATE 0.15 g/5 g; TITANIUM DIOXIDE 0.24 g/5 g
INACTIVE INGREDIENTS: DIMETHICONE 0.275 g/5 g; ALUMINUM HYDROXIDE 0.009 g/5 g

ACTIVE INGREDIENT

INGREDIENTS:

WATER, PROPYLENE GLYCOL, CYCLOMETHICONE, DIMETHICONE, TITANIUM DIOXIDE, ISOPROPYL PALMITATE, TALC, ETHYLHEXYL METHOXYCINNAMATE, BUTYLENE GLYCOL DICAPRYLATE/DICAPRATE, PRUNUS AMYGDALUS DIACIA (SWEET ALMOND) OIL, ETHYLHEXYL SALICYLATE, DIPENTAERYTHRITYL, HEXAHYDROXYSTEARATE/HEXASTEARATE/HEXAROSINATE, CETYL PEG/PPG-10/1 DIMETHICONE, ARBUTIN, ZINC OXIDE, POLYGLYCERYL-4 ISOSTEARATE, MAGNESIUM SULFATE, DIMETHICONE/VINYL DIMETHICONE CROSSPOLYMER, IRON OXIDES, SILICA, VINYL DIMETHICONE/METHICONE SILSESQUIOXANE CROSSPOLYER, PORTULACA OLERACEA EXTRACT, PIPER METHYSTICUM LEAF/ROOT/STEM EXTRACT, PHENOXYETHANOL, TRIHYDROXYSTEARIN, DISTEARDIMONIUM HECTORITE, GLYCOSYL TREMALOSE, ALUMINUM HYDROXIDE, ALUMINUM STEARATE, METHYLPARABEN, HYDROGENATED STARCH HYDROLYSATE, METHICONE, TOCOPHERYL ACETATE, HYDROGENATED LECITHIN, NELUMBO NUCIFERA FLOWER WATER, MADECASSOSIDE, CAMELLA SINENSIS LEAF EXTRACT, ALOE BARBEDENSIS LEAF JUICE, CHOLESTEROL, CERAMIDE 3, LYCIUM CHINENSE FRUIT EXTRACT, HELIANTHUS ANNUUS (SUNFLOWER) EXTRACT, SCHIZANDRA CHINENSIS FRUIT EXTRACT, HEDERA HELIX (IVY) EXTRACT, CORNUS OFFICINALIS FRUTI EXTRACT, FRAGRANCE, PROPYLPARABEN, BUTYLPARABEN, GLYCERIN, ADENOSINE, CAPRYLIC/CAPRIC TRIGLYCERIDE, TRICLOSAN, PHYTIC ACID, UBIQUNONE, BHT

DIRECTIONS:

Use it proper quantity on the area of your face like patting at the last step of skin care.